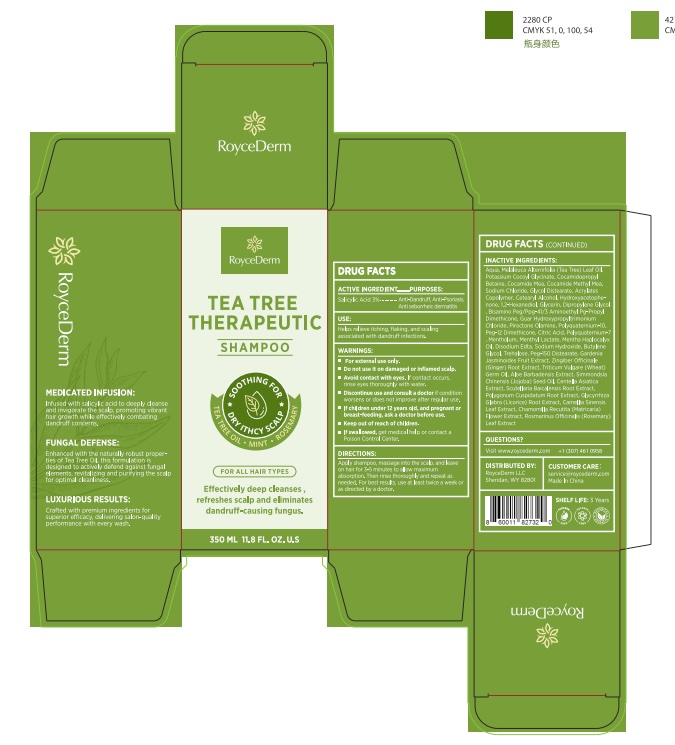 DRUG LABEL: RoyceDerm Tea Tree Therapeutic
NDC: 85424-012 | Form: GEL
Manufacturer: RoyceDerm LLC
Category: otc | Type: HUMAN OTC DRUG LABEL
Date: 20251219

ACTIVE INGREDIENTS: SALICYLIC ACID 3 mg/100 mL
INACTIVE INGREDIENTS: SODIUM BENZOATE; POTASSIUM SORBATE; CITRIC ACID; SODIUM LAURETH SULFATE; ALOE BARBADENSIS LEAF JUICE; MELALEUCA ALTERNIFOLIA (TEA TREE) LEAF OIL; PANTHENOL; SODIUM CHLORIDE; GLYCERIN; COCAMIDOPROPYL BETAINE

Initial Drug Listing - RoyceDerm Tea Tree Therapeutic Shampoo

ACTIVE INGREDIENT

Salicylic Acid 3%

PURPOSE

Anti-dandruff, anti-psoriasis, anti-seborrheic dermatitis

INDICATIONS AND USAGE

- Helps control dandruff
- Relieves itching, scaling, and flaking associated with dandruff

WARNINGS

For external use only

- Do not use it on damaged or inflamed scalp.
- Avoid contact with eyes. If contact occurs, rinse eyes thoroughly with water.

ASK DOCTOR

- If condition worsens or does not improve after regular use.
- If children under 12 years old, and pregnant or breast-feeding.
- If swallowed, get medical help or contact a posion control center.

Keep out of reach of Children.

DOSAGE AND ADMINISTRATION

Apply shampoo, massage into the scalp, and leave on hair for 3-5 minutes to allow maximum absorption. Then rinse thoroughly and repeat as needed. For best results, use at least twice a week or as directed by a doctor.

INACTIVE INGREDIENT

Aqua, Melaleuca Alternifolia (Tea Tree) Leaf Oil, Potassium Cocoyl Glycinate, Cocamidopropyl Betaine, Cocamide MEA, Cocamide Methyl MEA, Sodium Chloride, Glycol Distearate, Acrylates Copolymer, Cetearyl Alcohol, Hydroxyacetophenone, 1,2-Hexanediol, Glycerin, Dipropylene Glycol, Bisamino PEG/PPG-41/3 Aminoethyl PG-Propyl Dimethicone, Guar Hydroxypropyltrimonium Chloride, Piroctone Olamine, Polyquaternium-10, PEG-12 Dimethicone, Citric Acid, Polyquaternium-7, Mentholum, Menthyl Lactate, Mentha Haplocalyx Oil, Disodium EDTA, Sodium Hydroxide, Butylene Glycol, Trehalose, PEG-150 Distearate, Gardenia Jasminoides Fruit Extract, Zingiber Officinale (Ginger) Root Extract, Triticum Vulgare (Wheat) Germ Oil, Aloe Barbadensis Extract, Simmondsia Chinensis (Jojoba) Seed Oil, Centella Asiatica Extract, Scutellaria Baicalensis Root Extract, Polygonum Cuspidatum Root Extract, Glycyrrhiza Glabra (Licorice) Root Extract, Camellia Sinensis Leaf Extract, Chamomilla Recutita (Matricaria) Flower Extract, Rosmarinus Officinalis (Rosemary) Leaf Extract.

QUESTIONS

Visit www.roycederm.com
+1 (307) 461 0958